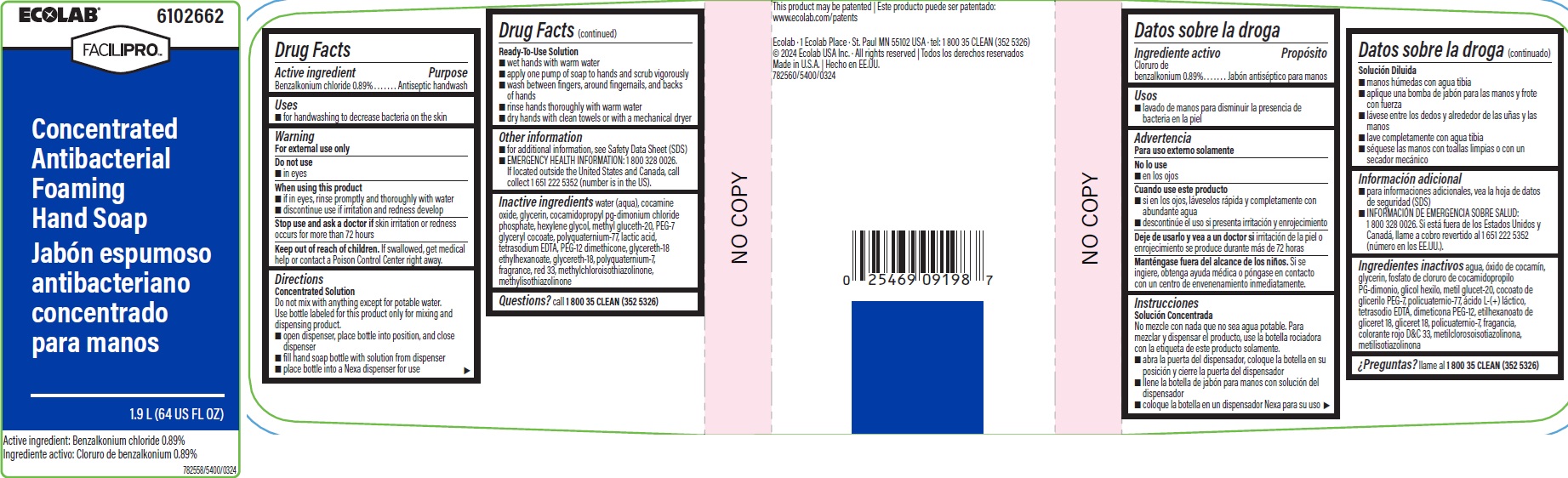 DRUG LABEL: Ecolab Inc.
NDC: 47593-513 | Form: SOLUTION
Manufacturer: Ecolab Inc.
Category: otc | Type: HUMAN OTC DRUG LABEL
Date: 20240712

ACTIVE INGREDIENTS: BENZALKONIUM CHLORIDE 8.9 mg/1 mL
INACTIVE INGREDIENTS: WATER; COCAMINE OXIDE; GLYCERIN; COCAMIDOPROPYL PG-DIMONIUM CHLORIDE PHOSPHATE; HEXYLENE GLYCOL; METHYL GLUCETH-20; PEG-7 GLYCERYL COCOATE; POLYQUATERNIUM-7 (70/30 ACRYLAMIDE/DADMAC; 1600000 MW); LACTIC ACID; EDETATE SODIUM; PEG-12 DIMETHICONE (300 CST); GLYCERETH-18 ETHYLHEXANOATE; GLYCERETH-18; D&C RED NO. 33; METHYLCHLOROISOTHIAZOLINONE; METHYLISOTHIAZOLINONE

Drug Facts

Active ingredient

Benzalkonium chloride 0.89%

Purpose

Antiseptic handwash

Uses

- for handwashing to decrease bacteria on the skin

Warnings

For external use only

Do not use

- in eyes

When using this product

- if in eyes, rinse promptly and thoroughly with water
- discontinue use if irritation and redness develop

Stop use and ask a doctor if skin irritation or redness occurs for more than 72 hours

Keep out of reach of children. If swallowed, get medical help or contact a Poison Control Center right away.

Directions Concentrated Solution

Do not mix with anything except for potable water.

Use bottle labeled for this product only for mixing and dispensing product.

- open dispenser, place bottle into position, and close dispenser
- fill hand soap bottle with solution from dispenser
- place bottle into a Nexa dispenser for use

Directions: Ready-To-Use Solution

- wet hands with warm water
- apply soap to hands and scrub vigorously
- wash between fingers, around fingernails, and back of hands
- rinse hands thoroughly with warm water
- dry hands with clean towel or with mechanical dryer

Other information

- for additional information, see Safety Data Sheet (SDS)
- EMERGENCY HEALTH INFORMATION: 1 800 328 0026. If located outside the United States and Canada, call collect 1 651 222 5352 (number in the US).

INACTIVE INGREDIENT

Inactive ingredients water (aqua), cocamine oxide, glycerin, cocamidopropyl pg-dimonium chloride phosphate, hexylene glycol, methyl gluceth-20, PEG-7 glyceryl cocoate, polyquaternium-77, lactic acid, tetrasodium EDTA, PEG-12 dimethicone, glycereth-18 ethylhexanoate, glycereth-18, polyquaternium-7, fragrance, red 33, methylchloroisothiazolinone, methylisothiazolinone

Questions? call 1800-35-CLEAN (352-5326)

Principal display panel and representative label

ECOLAB 6102662

FACILIPRO

Concentrated

Antibacterial

Foaming

Hand Soap

1.9L (64 US FL OZ)

Active ingredeint: Benzalkonium chloride 0.89%

Ecolab · 1 Ecolab Place · St. Paul MN 55102 USA · tel: 1 800 35 CLEAN (352 5326)

© 2024 Ecolab USA Inc. · All rights reserved

Made in U.S.A.

782560/5400/0324